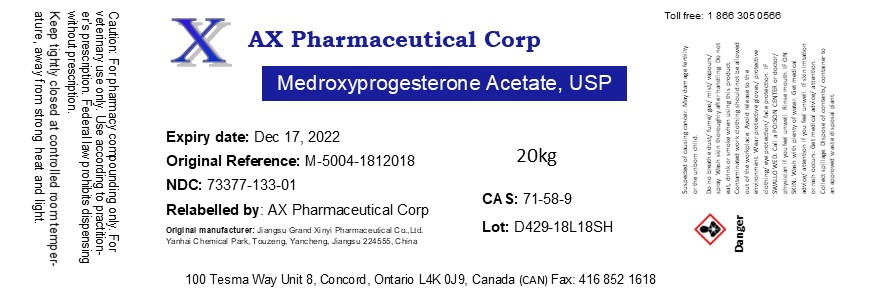 DRUG LABEL: Medroxyprogesterone Acetate
NDC: 73377-133 | Form: POWDER
Manufacturer: AX Pharmaceutical Corp
Category: other | Type: BULK INGREDIENT
Date: 20210603

ACTIVE INGREDIENTS: Medroxyprogesterone Acetate 1 kg/1 kg

Medroxyprogesterone Acetate